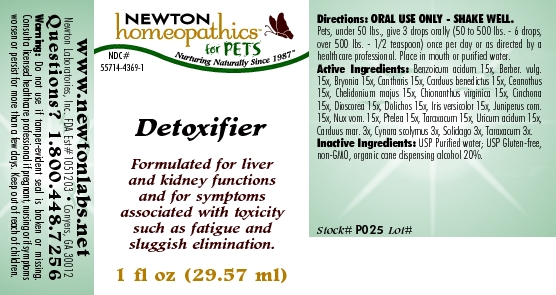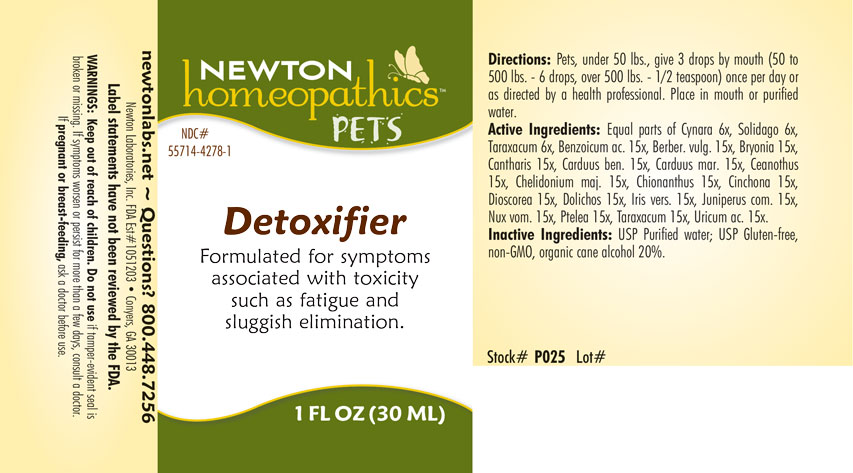 DRUG LABEL: Detoxifier
NDC: 55714-4369 | Form: LIQUID
Manufacturer: Newton Laboratories, Inc.
Category: homeopathic | Type: OTC ANIMAL DRUG LABEL
Date: 20190114

ACTIVE INGREDIENTS: Benzoic Acid 15 [hp_X]/1 mL; Berberis Vulgaris Root Bark 15 [hp_X]/1 mL; Bryonia Alba Root 15 [hp_X]/1 mL; Lytta Vesicatoria 15 [hp_X]/1 mL; Centaurea Benedicta 15 [hp_X]/1 mL; Ceanothus Americanus Leaf 15 [hp_X]/1 mL; Chelidonium Majus 15 [hp_X]/1 mL; Chionanthus Virginicus Bark 15 [hp_X]/1 mL; Cinchona Officinalis Bark 15 [hp_X]/1 mL; Dioscorea Villosa Tuber 15 [hp_X]/1 mL; Mucuna Pruriens Fruit Trichome 15 [hp_X]/1 mL; Iris Versicolor Root 15 [hp_X]/1 mL; Juniper Berry 15 [hp_X]/1 mL; Strychnos Nux-vomica Seed 15 [hp_X]/1 mL; Ptelea Trifoliata Bark 15 [hp_X]/1 mL; Taraxacum Officinale 15 [hp_X]/1 mL; Uric Acid 15 [hp_X]/1 mL; Cynara Scolymus Leaf 3 [hp_X]/1 mL; Solidago Virgaurea Flowering Top 3 [hp_X]/1 mL
INACTIVE INGREDIENTS: Alcohol

Detoxifier

INDICATIONS & USAGE SECTION

Detoxifier Formulated for symptoms associated with toxicity such as fatigue and sluggish elimination.

DOSAGE & ADMINISTRATION SECTION

Directions: Pets, under 50 lbs., give 3 drops by mouth (50 to 500 lbs. - 6 drops, over 500 lbs. - 1/2 teaspoon) once per day or as directed by a health professional. Place in mouth or purified water.

OTC - ACTIVE INGREDIENT SECTION

Equal parts of Cynara scolymus 6x, Solidago 6x, Taraxacum 6x, Benzoicum acidum 15x, Berber. vulg.15x, Bryonia 15x, Cantharis 15x, Carduus benedictus 15x, Carduus mar. 15x, Ceanothus 15x, Chelidonium majus 15x, Chionanthus virginica 15x, Cinchona 15x, Dioscorea 15x, Dolichos 15x, Iris versicolor 15x, Juniperus com.15x, Nux vom. 15x, Ptelea 15x, Taraxacum 15x, Uricum acidum 15x.

OTC - PURPOSE SECTION

Formulated for symptoms associated with toxicity such as fatigue and sluggish elimination.

INACTIVE INGREDIENT SECTION

Inactive Ingredients: USP Purified Water; USP Gluten-free, non-GMO, organic cane alcohol 20%.

QUESTIONS SECTION

newtonlabs.net Questions? 1.800.448.7256
Newton Laboratories, Inc. FDA Est # 1051203 - Conyers, GA 30013
Labels have not been reviewed by the FDA.

WARNINGS SECTION

WARNINGS: Keep out of reach of children. Do not use if tamper-evident seal is broken or missing. If symptoms worsen or persist for more than a few days, consult a doctor. If pregnant or breast-feeding, ask a doctor before use.

OTC - PREGNANCY OR BREAST FEEDING SECTION

If pregnant or breast-feeding, ask a doctor before use.

OTC - KEEP OUT OF REACH OF CHILDREN SECTION

Keep out of reach of children.